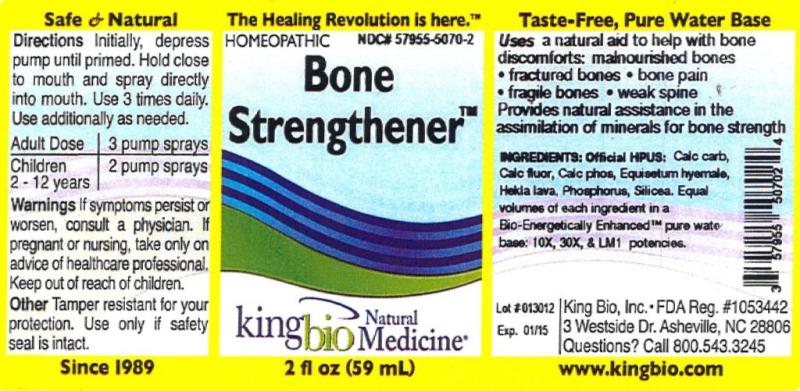 DRUG LABEL: Bone Strengthener
NDC: 57955-5070 | Form: LIQUID
Manufacturer: King Bio Inc.
Category: homeopathic | Type: HUMAN OTC DRUG LABEL
Date: 20120410

ACTIVE INGREDIENTS: OYSTER SHELL CALCIUM CARBONATE, CRUDE 10 [hp_X]/59 mL; CALCIUM FLUORIDE 10 [hp_X]/59 mL; TRIBASIC CALCIUM PHOSPHATE 10 [hp_X]/59 mL; EQUISETUM HYEMALE 10 [hp_X]/59 mL; HEKLA LAVA 10 [hp_X]/59 mL; PHOSPHORUS 10 [hp_X]/59 mL; SILICON DIOXIDE 10 [hp_X]/59 mL
INACTIVE INGREDIENTS: WATER

Bone Strengthener

Active Ingredients

Official HPUS: Calcarea carbonica, Calcarea fluorica, Calcarea phosphorica, Equisetum hyemale, Hekla lava, Phosphorus, and silicea.

Reference image bonestrengthener.jpg

Inactive Ingredient

Equal volumes of each ingredient in a Bio-Energetically Enhanced pure water base: 10X, 30X, and LM1 potencies.

Reference image bonestrengthener.jpg

Purpose

Uses a natural aid to help with bone discomforts:

- malnourished bones
- fractured bones
- bone pain
- fragile bones
- weak spine

Provides natural assistance in the assimilation of minerals for bone strength.
Reference image bonestrengthener.jpg

Dosage and Administration

Directions Initially, depress pump until primed. Hold close to mouth and spray directly into mouth. Use 3 times daily. Use additionally as needed.

Adult Dose 3 pump sprays

Children 2-12 years 2 pump sprays

Reference image bonestrengthener.jpg

Warnings

If symptoms persist or worsen, consult a physician. If pregnant or nursing, take only on advice of healthcare professional. Keep out of reach of children.

Other: Tamper resistant for your protection. Use only if safety seal intact.

Reference image bonestrengthener.jpg

Keep out of reach of children.

Reference image bonestrengthener.jpg

Indications and Usage

Uses a natural aid to help with bone discomforts: malnourished bones, fractured bones, bone pain, fragile bones, weak spine.

Provides natural assistance in the assimilation of minerals for bone strength.

Reference image bonestrengthener.jpg

PACKAGE LABEL

King Bio, Inc.

3 Westside Drive

Asheville, NC 28806

Questions? Call 800.543.3245

www.kingbio.com

Reference image bonestrengthener.jpg